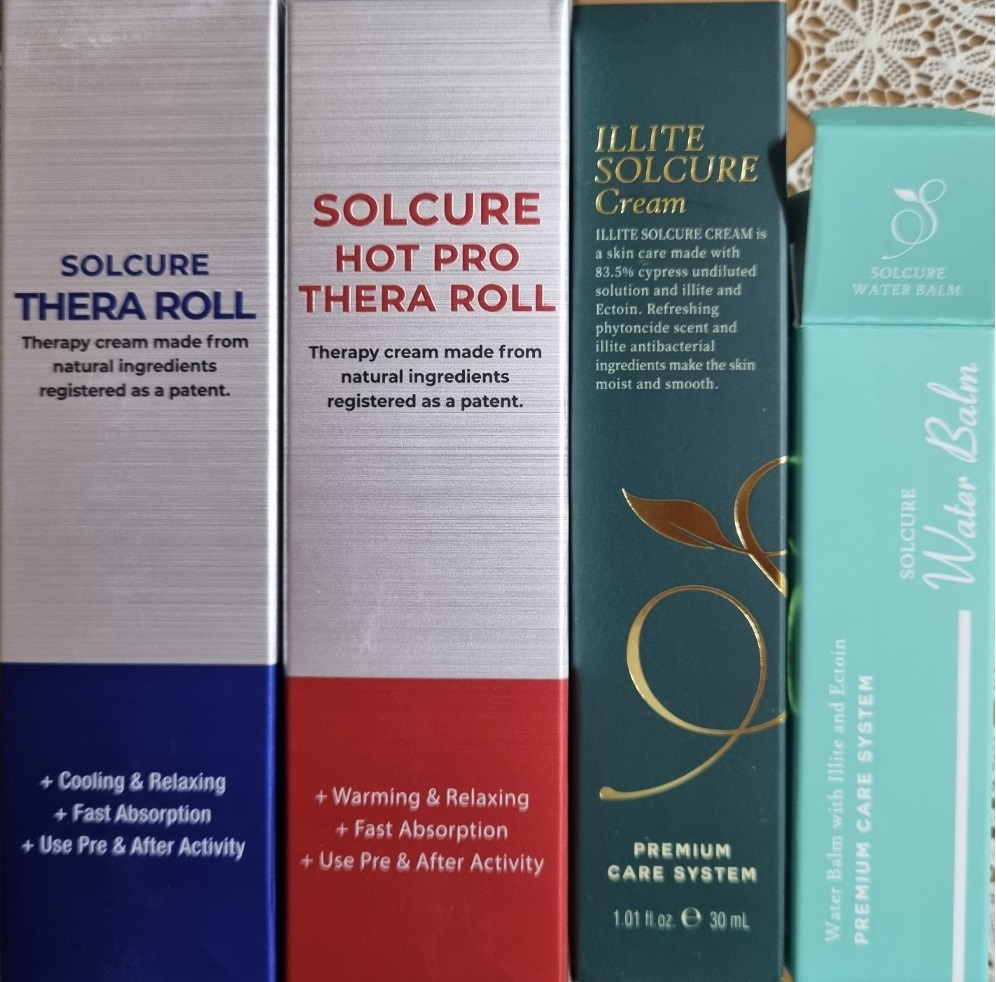 DRUG LABEL: Solcure Thera Roll Hot Pro
NDC: 83235-0002 | Form: LIQUID
Manufacturer: Erae Natural Life
Category: otc | Type: HUMAN OTC DRUG LABEL
Date: 20230201

ACTIVE INGREDIENTS: MENTHOL 1 g/100 mL
INACTIVE INGREDIENTS: WATER; GLYCERIN

Drug Facts

ACTIVE INGREDIENT

menthol

INACTIVE INGREDIENT

Water
Ethanol
Chamaecyparis Obtusa Water
Dipropylene Glycol
Glycerin
Illite Extract
Butylene Glycol
Vincetoxicum Atratum Extract
Sodium Polyacrylate
Laureth-7
C13-14 Isoalkane
Vanillyl Butyl Ether
Fragrance

PURPOSE

therapy by warming & relaxing

keep out or reach of the children

INDICATIONS AND USAGE

Apply an appropriate amount as if massaging before and after exercise (except for the face and sensitive body parts)

WARNINGS

This product is for exeternal use only. Do not use for internal use
Storage and handling precautions
If possible, avoid direct sunlight and store in cool and area of low humidity in order to maintain the quality of the product and avoid misuse
Avoid placing the product near fire and store out in reach of children

- consult a physician in case of abnormal symptoms, such as red spots, swelling or itching, or side effects in the areas of application due to direct light during or after using the product

- do not use on wounded area

DOSAGE AND ADMINISTRATION

for external use only